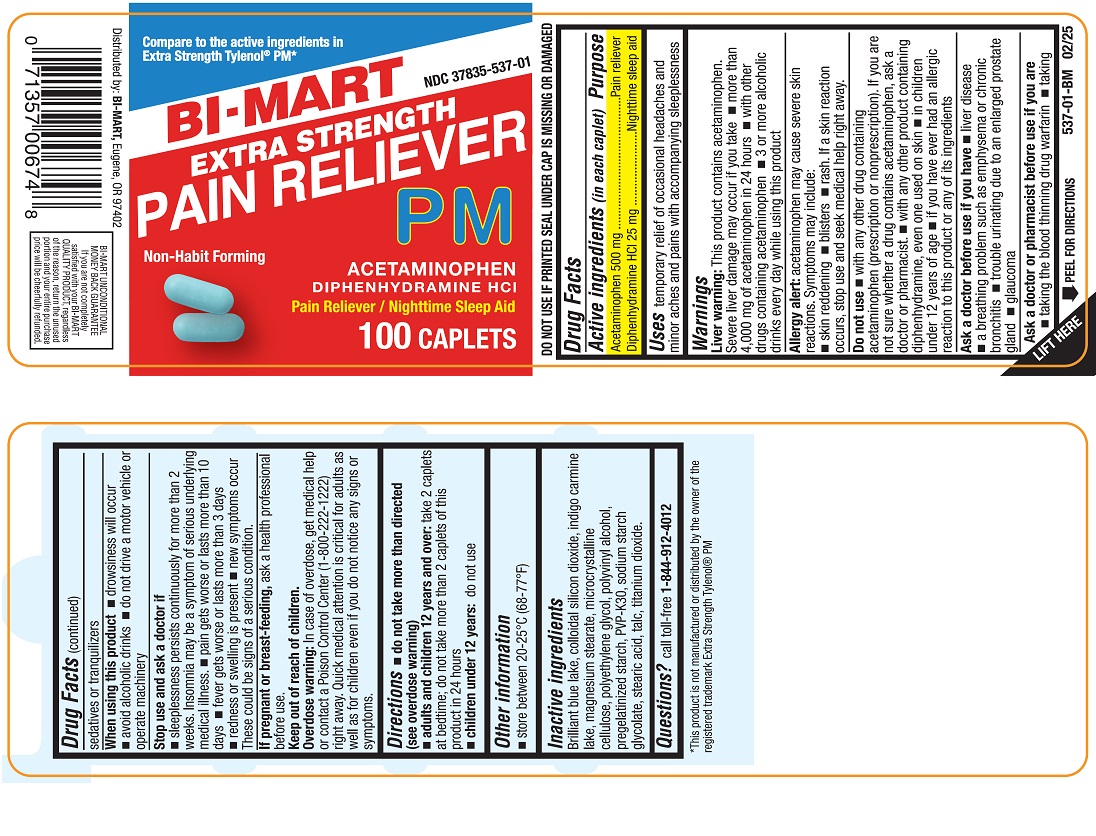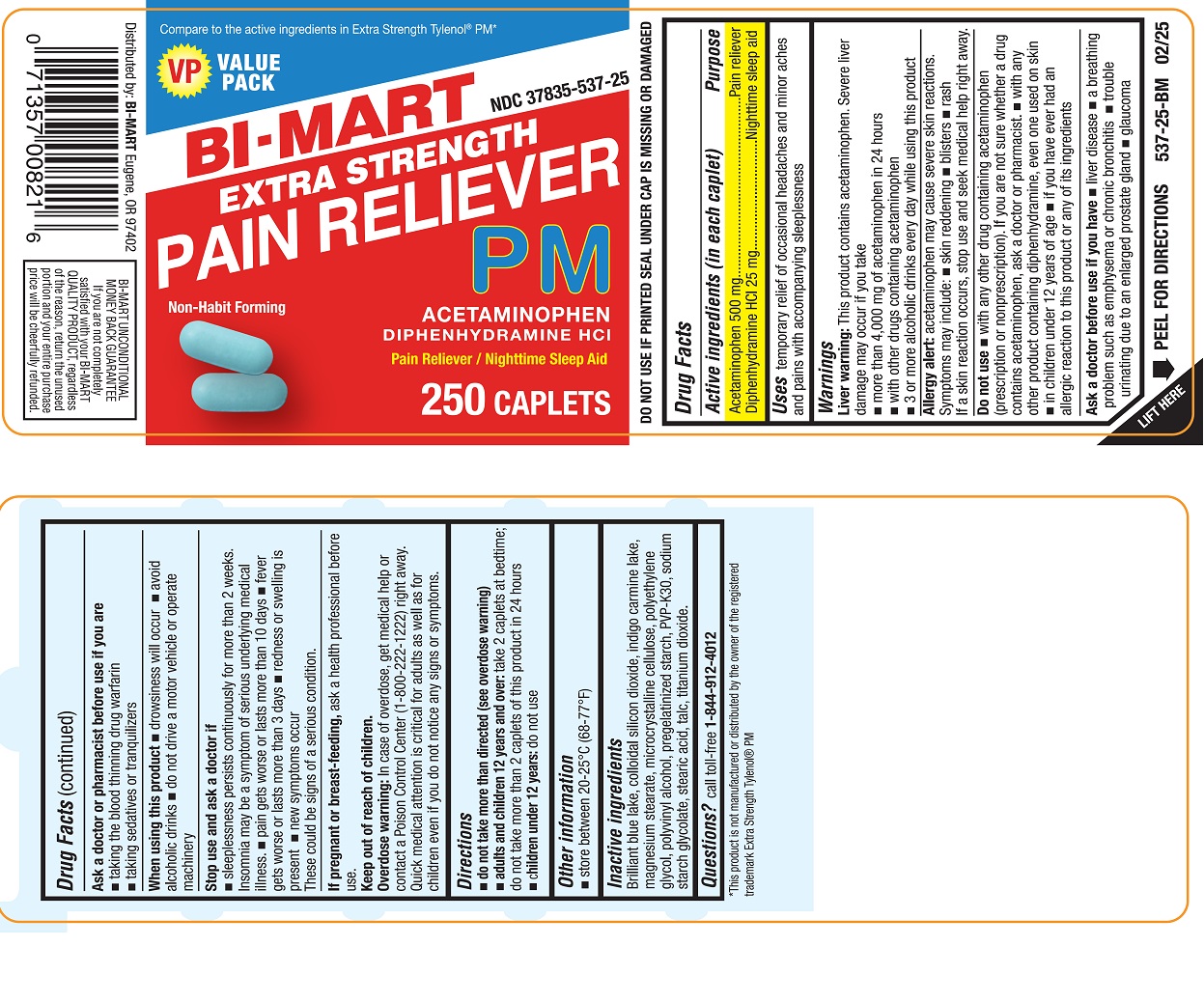 DRUG LABEL: Acetaminophen and Diphenhydramine Hydrochloride
NDC: 37835-537 | Form: TABLET
Manufacturer: Bi-Mart
Category: otc | Type: HUMAN OTC DRUG LABEL
Date: 20250702

ACTIVE INGREDIENTS: ACETAMINOPHEN 500 mg/1 1; DIPHENHYDRAMINE 25 mg/1 1
INACTIVE INGREDIENTS: FD&C BLUE NO. 1; SILICON DIOXIDE; MAGNESIUM STEARATE; MICROCRYSTALLINE CELLULOSE; POLYETHYLENE GLYCOL, UNSPECIFIED; POLYVINYL ALCOHOL; STARCH, PREGELATINIZED CORN; POVIDONE K30; SODIUM STARCH GLYCOLATE TYPE A CORN; STEARIC ACID; TALC; TITANIUM DIOXIDE

Drug Facts

ACTIVE INGREDIENT

Active ingredients (in each caplet) | Purpose
Acetaminophen 500 mg | Pain reliever
Diphenhydramine HCl 25 mg | Nighttime sleep aid

Uses

temporary relief of occasional headaches and minor aches and pains with accompanying sleeplessness

Warnings

Liver warning

This product contains acetaminophen. Severe liver damage may occur if you take

- more than 4,000 mg of acetaminophen in 24 hours
- with other drugs containing acetaminophen
- 3 or more alcoholic drinks every day while using this product

Allergy alert:

acetaminophen may cause severe skin reactions.

Symptoms may include:

■ skin reddening ■ blisters ■ rash

If a skin reaction occurs, stop use and seek medical help right away

Do not use

- with any other drug containing acetaminophen (prescription or nonprescription). If you are not sure whether a drug contains acetaminophen, ask a doctor or pharmacist.
- with any product containing diphenhydramine, even one used on skin
- in children under 12 years of age
- if you have ever had an allergic reaction to this product or any of its ingredients

Ask a doctor before use if you have

- liver disease
- a breathing problem such as emphysema or chronic bronchitis
- trouble urinating due to an enlarged prostate gland
- glaucoma

Ask a doctor or pharmacist before use if you are

- taking the blood thinning drug warfarin
- taking sedatives or tranquilizers

When using this product

- drowsiness will occur
- avoid alcoholic drinks
- do not drive a motor vehicle or operate machinery

Stop use and ask a doctor if

- sleeplessness persists continuously for more than 2 weeks. Insomnia may be a symptom of serious underlying medical illness.
- pain gets worse or lasts more than 10 days
- fever gets worse or lasts more than 3 days
- redness or swelling is present
- new symptoms occur

These could be signs of a serious condition.

PREGNANCY OR BREAST FEEDING

If pregnant or breast-feeding,ask a health professional before use.

Keep out of reach of children.

Overdose warning

In case of overdose, get medical help or contact a Poison Control Center (1-800-222-1222) right away. Quick medical attention is critical for adults as well as for children even if you do not notice any signs or symptoms.

Directions

- do not take more than directed (see overdose warning)
- adults and children 12 years and over:take 2 caplets at bedtime; do not take more than 2 caplets of this product in 24 hours
- children under 12 years:do not use

Other information

- store between 20-25°C (68-77°F)
- DO NOT USE IF PRINTED SEAL UNDER CAP IS MISSING OR DAMAGED

Inactive ingredients

brilliant blue lake, colloidal silicon dioxide, indigo carmine lake, magnesium stearate, microcrystalline cellulose, polyethylene glycol, polyvinyl alcohol, pregelatinized starch, PVP-K30, sodium starch glycolate, stearic acid, talc, titanium dioxide.

Questions?

call toll free 1-844-912-4012

PRINCIPAL DISPLAY PANEL-100 Count

NDC 37835-537-01

Compare to the active ingredients in Extra Strength Tylenol®PM*

EXTRA STRENGTH PAIN RELIEVER PM

Acetaminophen, Diphenhydramine HCl

Pain Reliever / Nighttime Sleep Aid

100 Caplets

*This product is not manufactured or distributed by the owner of the registered trademark Extra Strength Tylenol®PM.

Distributed by:

BI-MART

Eugene, OR 97402

PRINCIPAL DISPLAY PANEL-250 Count

NDC 37835-537-25

Compare to the active ingredients in Extra Strength Tylenol®PM*

EXTRA STRENGTH PAIN RELIEVER PM

Acetaminophen, Diphenhydramine HCl

Pain Reliever / Nighttime Sleep Aid

250 Caplets

*This product is not manufactured or distributed by the owner of the registered trademark Extra Strength Tylenol®PM.

Distributed by:

BI-MART

Eugene, OR 97402